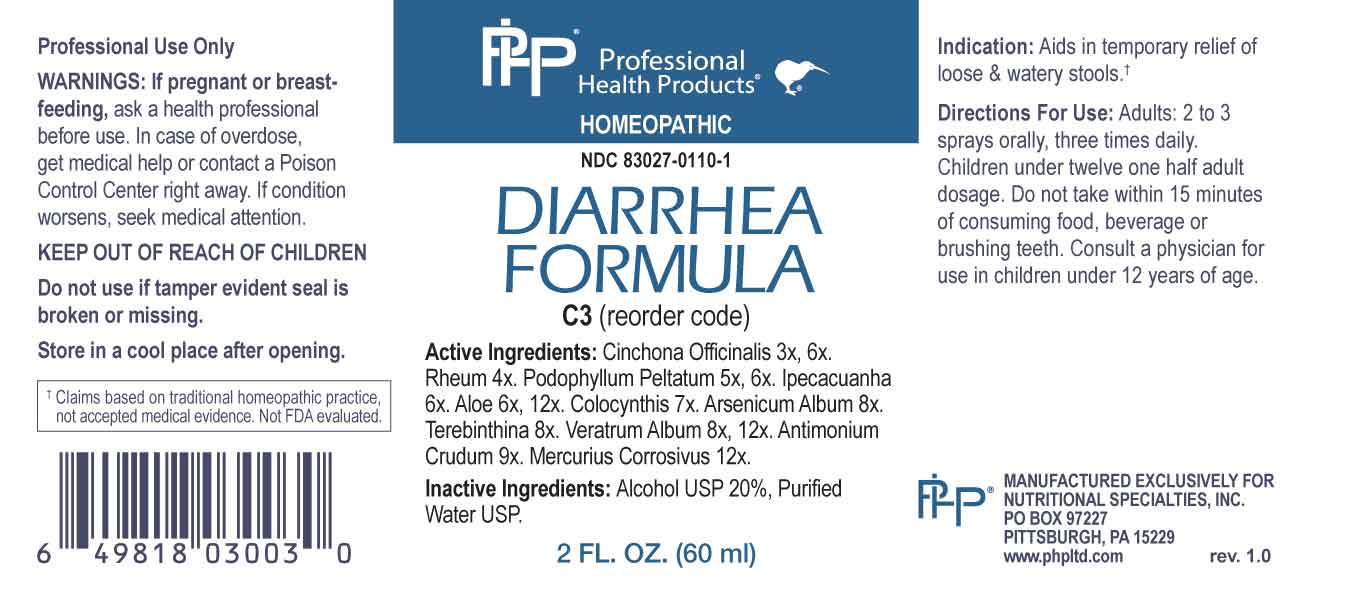 DRUG LABEL: Diarrhea Formula
NDC: 83027-0110 | Form: SPRAY
Manufacturer: Nutritional Specialties, Inc.
Category: homeopathic | Type: HUMAN OTC DRUG LABEL
Date: 20231005

ACTIVE INGREDIENTS: CINCHONA OFFICINALIS BARK 3 [hp_X]/1 mL; RHEUM PALMATUM ROOT 4 [hp_X]/1 mL; PODOPHYLLUM 5 [hp_X]/1 mL; IPECAC 6 [hp_X]/1 mL; ALOE 6 [hp_X]/1 mL; CITRULLUS COLOCYNTHIS FRUIT PULP 7 [hp_X]/1 mL; ARSENIC TRIOXIDE 8 [hp_X]/1 mL; TURPENTINE OIL 8 [hp_X]/1 mL; VERATRUM ALBUM ROOT 8 [hp_X]/1 mL; ANTIMONY TRISULFIDE 9 [hp_X]/1 mL; MERCURIC CHLORIDE 12 [hp_X]/1 mL
INACTIVE INGREDIENTS: WATER; ALCOHOL

DRUG FACTS:

ACTIVE INGREDIENTS:

Cinchona Officinalis 3X, 6X, Rheum 4X, Podophyllum Peltatum 5X, 6X, Ipecacuanha 6X, Aloe 6X, 12X, Colocynthis 7X, Arsenicum Album 8X, Terebinthina 8X, Veratrum Album 8X, 12X, Antimonium Crudum9X, Mercurius Corrosivus 12X.

PURPOSE:

Aids in temporary relief of loose & watery stools.†

†Claims based on traditional homeopathic practice, not accepted medical evidence. Not FDA evaluated.

WARNINGS:

Professional Use Only

If pregnant or breast-feeding, ask a health professional before use.

In case of overdose, get medical help or contact a Poison Control Center right away.

If condition worsens, seek medical attention.

KEEP OUT OF REACH OF CHILDREN

Do not use if tamper evident seal is broken or missing.

Store in a cool place after opening

KEEP OUT OF REACH OF CHILDREN:

In case of overdose, get medical help or contact a Poison Control Center right away.

DIRECTIONS:

Adults: 2 to 3 sprays orally, three times daily. Children under twelve one half adult dosage. Do not take within 15 minutes of consuming food, beverage or brushing teeth. Consult a physician for use in children under 12 years of age.

INDICATIONS:

Aids in temporary relief of loose & watery stools.†

†Claims based on traditional homeopathic practice, not accepted medical evidence. Not FDA evaluated.

INACTIVE INGREDIENTS:

Alcohol USP 20%, Purified Water USP.

QUESTIONS:

MANUFACTURED EXCLUSIVELY FOR

NUTRITIONAL SPECIALTIES, INC.

PO BOX 97227

PITTSBURG, PA 15229

www.phpltd.com

PACKAGE LABEL.PRINCIPAL DISPLAY PANEL

Professional

Health Products

HOMEOPATHIC

NDC 83027-0110-1

DIARRHEA

FORMULA

2 FL. OZ (60 ml)